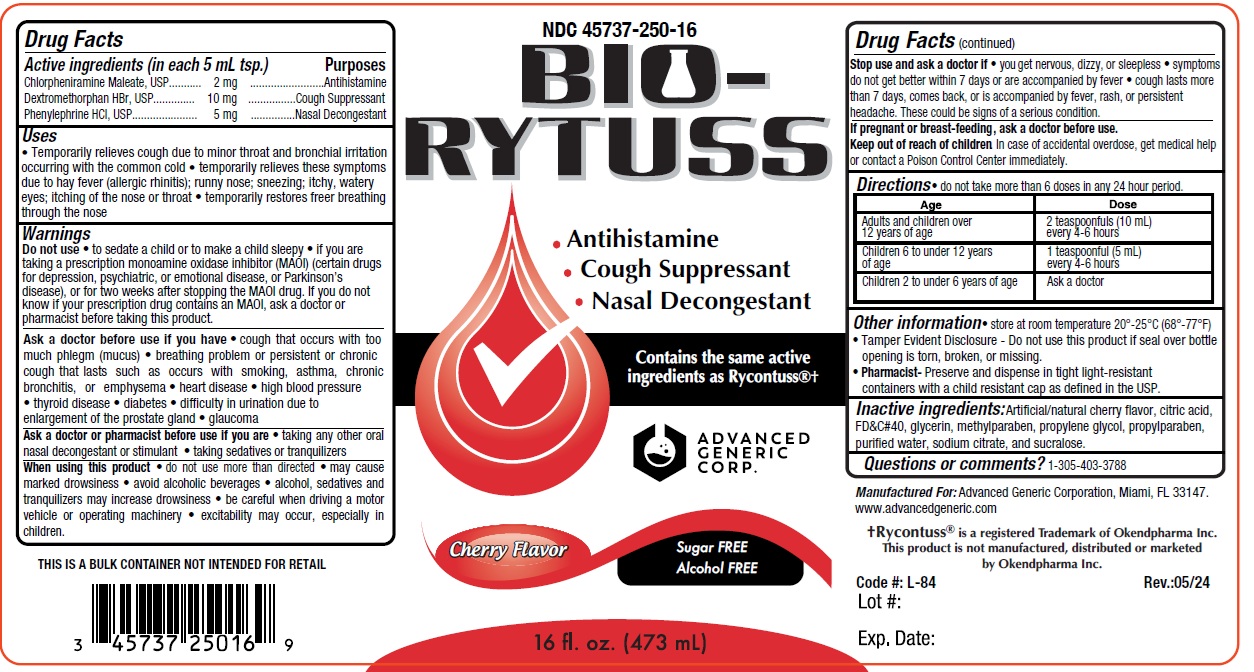 DRUG LABEL: BIO-RYTUSS
NDC: 45737-250 | Form: LIQUID
Manufacturer: Advanced Generic Corporation
Category: otc | Type: HUMAN OTC DRUG LABEL
Date: 20251230

ACTIVE INGREDIENTS: CHLORPHENIRAMINE MALEATE 2 mg/5 mL; DEXTROMETHORPHAN HYDROBROMIDE 10 mg/5 mL; PHENYLEPHRINE HYDROCHLORIDE 5 mg/5 mL
INACTIVE INGREDIENTS: CITRIC ACID MONOHYDRATE; METHYLPARABEN; PROPYLPARABEN; SODIUM CITRATE; SUCRALOSE; FD&C RED NO. 40; PROPYLENE GLYCOL; WATER

AGC-BioRYTuss 250

Active ingredients (in each 5 mL tsp.) Purpose

Chlorpheniramine Maleate 2 mg Antihistamine

Dextromethorphan Hydrobromide 10 mg Cough Suppressant

Phenylephrine Hydrochloride 5 mg Nasal Decongestant

Purpose

Antihistamine

Cough Suppressant

Nasal Decongestant

Warnings

Ask doctor before use if you have

- Cough that occurs with too much phlegm (mucus), or a breathing problem or persitent or chronic cough that lasts such as occurs with smoking, asthma, chronic bronchitis or emphysema.
- Heart disease
- High blood pressure
- Thyroid Disease
- Diabetes
- Difficulty in urinating due to enlarged prostate gland
- Glaucoma

Ask doctor or pharmacist before use if you are taking any other oral nasal decongestant or stimulant; taking sedatives or tranquilizers.

When using this product

- Do not use more than directed
- May cause marked drowsiness; avoid alcohol beverages; alcohol, sedatives and tranquilizers may increase drowsiness.
- Be careful when driving a motor vehicle or operating machinery; excitability may occur, especially with children.

Do not use

- To sedate a child or to make a child sleepy
- If you are now taking a prescription monoamine oxidase inhibitor (MAOI) (certain drugs for depression, psychiatric, or emotional conditions or Parkinson's disease), or for 2 weeks after stopping the MAOI drug. If you do not know if you are taking a prescription that contains an MAOI, ask your doctor or pharmacist before taking this product

Stop use and ask a doctor if you

- you get nervous, dizzy or sleepless
- symptoms do not get better within 7 days or are accompanied by fever
- cough lasts more than 7 days, comes back, or is accompanied by fever, rash or persistent headaches. These could be signs of a serious condition.

Keep out of reach of children.In case of overdose, get medical help or contact a Poison Control Center immediately

PREGNANCY OR BREAST FEEDING

If pregnant or breast-feeding,ask a doctor before use

DOSAGE AND ADMINISTRATION

Directionsdo not take more than 6 doses in any 24 hour period

adults and children 12 years of age | 2 teaspoonful (10 mL) every 4-6 hours
children 6 to under 12 years of age | 1 teaspoonful (5 mL) every 4-6 hours
children 2 to under 6 years of age | 1/2 teaspoonful (2.5 mL); every 4-6 hours

Uses

- temporarily relieves cough due to minor throat and bronchial irritation occurring with a cold, and nasal congestion due to the common cold, hay fever or other upper respiratory allergies
- temporarily relieves these symptoms due to hay fever (allergic rhinitis); runny nose; sneezing; itchy watery eyes; itching of the nose or throat
- temporarily restores freer beathing through the nose.

Inactive ingredients

Citric acid, FD&C Red #40, flavor, methylparaben, propylene glycol, propylparaben, purified water, Sodium citrate, sucralose.

Questions or comments?

1-305-403-3788